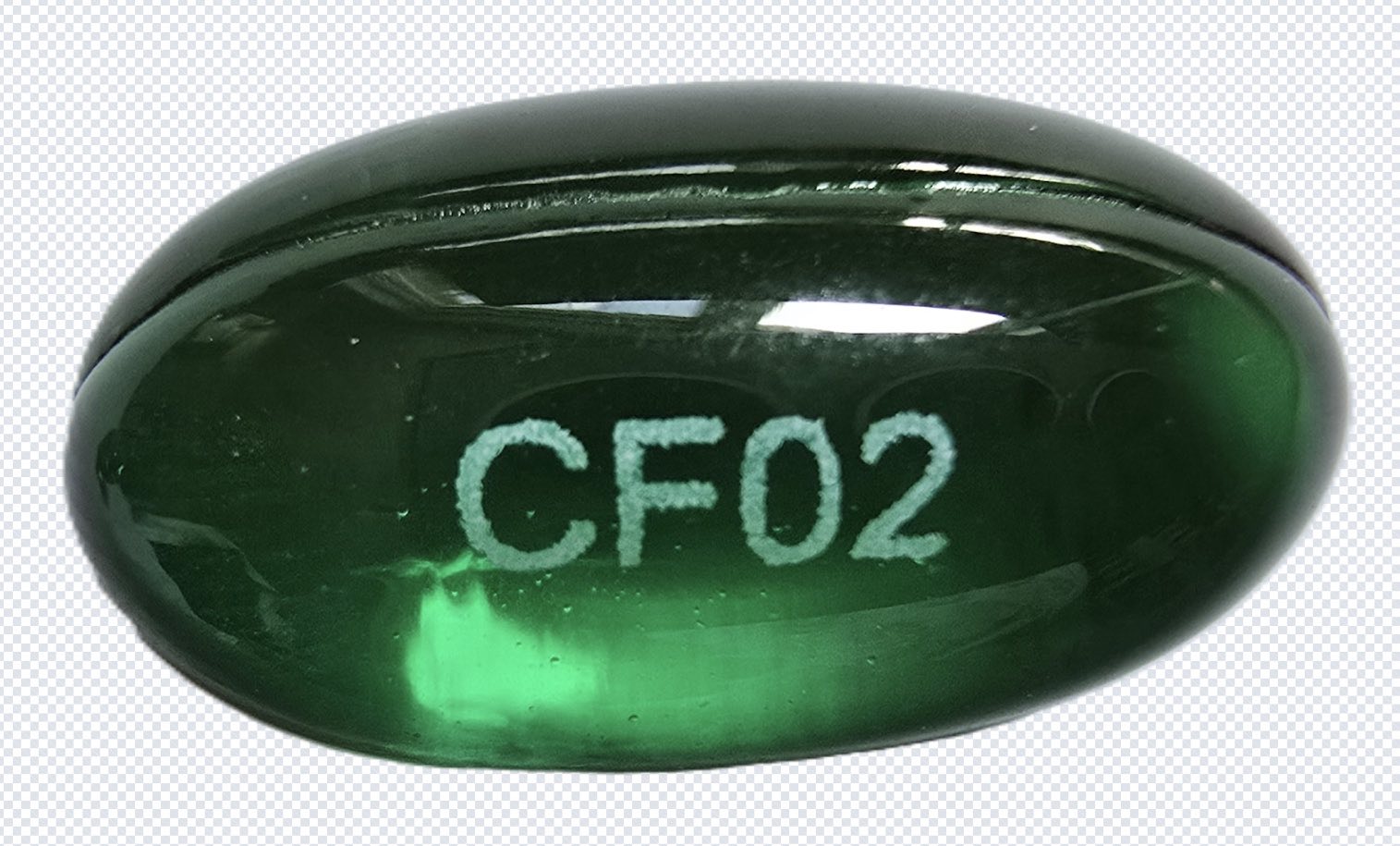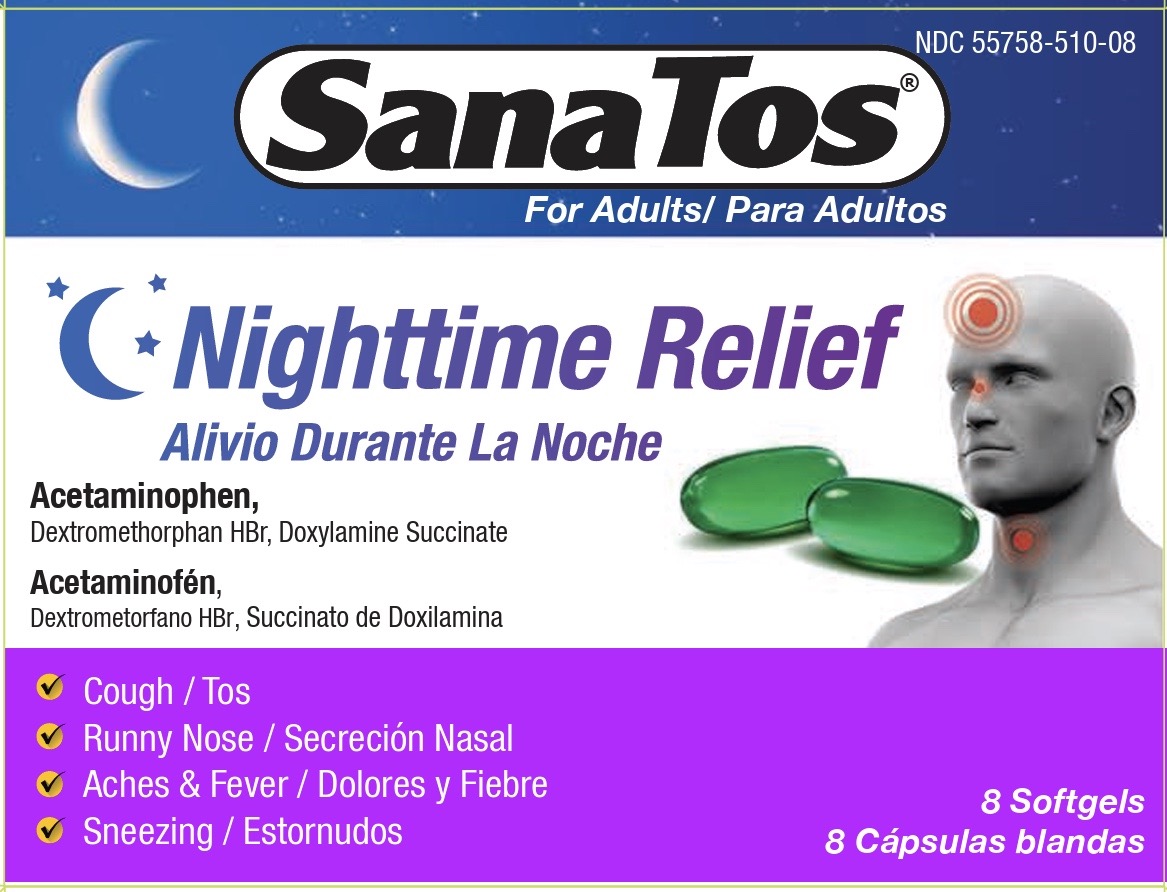 DRUG LABEL: Sanatos
NDC: 55758-510 | Form: CAPSULE, LIQUID FILLED
Manufacturer: Pharmadel LLC
Category: otc | Type: HUMAN OTC DRUG LABEL
Date: 20250902

ACTIVE INGREDIENTS: ACETAMINOPHEN 325 mg/1 1; DEXTROMETHORPHAN HYDROBROMIDE 15 mg/1 1; DOXYLAMINE SUCCINATE 6.25 mg/1 1
INACTIVE INGREDIENTS: SORBITAN; FD&C BLUE NO. 1; D&C YELLOW NO. 10; GELATIN; GLYCERIN; POLYETHYLENE GLYCOL 400; POVIDONE K30; PROPYLENE GLYCOL; WATER; SORBITOL

Sanatos Nightime Softgel (HHH Pharma)

Drug Facts

.

Active Ingredients and Purposes

.

PURPOSE

Active ingredients (in each softgel) | Purposes
Acetaminophen 325 mg.............. | Pain reliever/ fever reducer
Dextromethorphan HBr 15 mg ...... | Cough suppressant
Doxylamine succinate 6.25 mg ..... | Antihistamine

Uses

Temporarily relieves cough-cold symptoms

- cough due to minor throat and bronchial irritation
- headache
- minor aches and pains
- runny nose
- sneezing
- itching of the nose or throat
- itchy, watery eyes due to hay fever
- temporarily reduces fever

Warnings

Liver warning:This product contains acetaminophen. Severe liver damage may occur if you take

- more than 8 softgels in 24 hours,which is the maximum daily amount for this product
- with other drugs containing acetaminophen
- 3 or more alcoholic drinks daily while using this product

Allergy alert: Acetaminophenmay cause severe skin reactions. Symptoms may include:

- skin reddening
- blisters
- rash

If a skin reaction occurs, stop use and seek medical help right away.

Do not use

- with any other drug containing acetaminophen (prescription or nonprescription). If you are not sure whether a drug contains acetaminophen, ask a doctor or pharmacist.
- if you are now taking a prescription monoamine oxidase inhibitor (MAOI) (certain drugs for depression, psychiatric or emotional conditions, or Parkinson's disease), or for 2 weeks after stopping the MAOI drug. If you do not know if your prescription drug contains an MAOI, ask a doctor or pharmacist before taking this product.

Ask a doctor before use if you have

- liver disease
- glaucoma
- a cough that is accompanied by excessive phlegm (mucus)
- a persistent or chronic cough as occurs with smoking, asthma or emphysema
- a breathing problem such as emphysema or chronic bronchitis
- difficulty urinating due to enlargement of the prostate gland

Ask a doctor or pharmacist before use if you are

- taking sedatives or tranquilizers
- taking the blood thinning drug warfarin

When using this product

- may cause marked drowsiness
- excitability may occur, especially in children
- alcohol, sedatives and tranquilizers may increase drowsiness effect
- avoid alcoholic drinks when taking this product
- use caution when driving a motor vehicle or operating machinery

Stop use and ask a doctor if

- pain or cough gets worse or lasts more than 7 days
- fever gets worse or lasts more than 3 days
- redness or swelling is present
- new symptoms occur
- cough comes back or occurs with a rash or a persistent headache that lasts.

These could be signs of a serious condition.

If pregnant or breast-feeding,

ask a health professional before use.

KEEP OUT OF REACH OF CHILDREN.

In case of accidental overdose, get medical help or contact a Poison Control Center right away. Prompt medical attention is critical for adults as well as for children even if you do not notice any signs or symptoms.

Directions

Age | Dose
adults and children 12 years and older | 2 softgels every 6 hours, do not exceed 8 softgels in a 24 hour period
children 4 to under 12 years | consult a doctor
children under 4 years | do not use

Other information

- store between 68-77°F (20-25°C)
- avoid excessive heat
- do not use if blister pack is punctured or torn

Inactive ingredients

D&C yellow #10, FD&C blue #1, gelatin, glycerin, polyethylene glycol 400, povidone k-30, propylene glycol, sorbitol sorbitan solution, water

Questions or comments?

+1-866-359-3478(M-F) 9 AM - 5 PM EST or www.pharmadel.com

Dist by/ por:

PHARMADEL LLC

New Castle, DE 19720

www.pharmadel.com